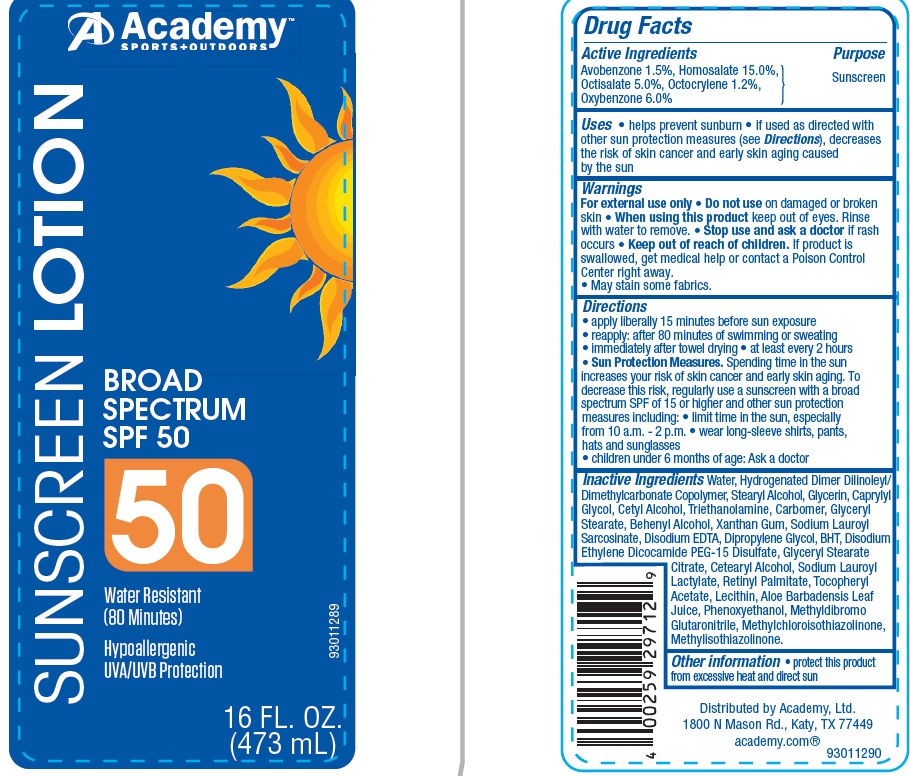 DRUG LABEL: Academy SPF 50
                        
NDC: 59054-880 | Form: LOTION
Manufacturer: ACADEMY, LTD
Category: otc | Type: HUMAN OTC DRUG LABEL
Date: 20160720

ACTIVE INGREDIENTS: AVOBENZONE 1.5 g/100 g; HOMOSALATE 15 g/100 g; OCTISALATE  5 g/100 g; OCTOCRYLENE 1.2 g/100 g; OXYBENZONE 6 g/100 g
INACTIVE INGREDIENTS: WATER; STEARYL ALCOHOL; GLYCERIN; CAPRYLYL GLYCOL; CETYL ALCOHOL; TROLAMINE; CARBOXYPOLYMETHYLENE; GLYCERYL MONOSTEARATE; DOCOSANOL; XANTHAN GUM; SODIUM LAURYL SARCOSINATE; EDETATE DISODIUM; DIPROPYLENE GLYCOL; BUTYLATED HYDROXYTOLUENE; DISODIUM ETHYLENE DICOCAMIDE PEG-15 DISULFATE; GLYCERYL STEARATE CITRATE; CETOSTEARYL ALCOHOL; SODIUM LAUROYL LACTYLATE; VITAMIN A PALMITATE; .ALPHA.-TOCOPHEROL ACETATE; ALOE VERA LEAF; PHENOXYETHANOL; METHYLDIBROMO GLUTARONITRILE; METHYLCHLOROISOTHIAZOLINONE; METHYLISOTHIAZOLINONE

Drug Facts

Active Ingredients

AVOBENZONE 1.5%, HOMOSALATE 15.0%, OCTISALATE 5.0%, OCTOCRYLENE 1.2%,

OXYBENZONE 6.0%

Purpose

Sunscreen

Uses

- helps prevent sunburn
- if used as directed with other sun protection measures (See Directions), decreases the risk of skin cancer and early skin aging caused by the sun

Warning

For external use only

Do not use

on damaged or broken skin

When using this product

keep out of eyes. Rinse with water to remove.

Stop use and ask a doctor

if rash occurs

Keep out of reach of children.

If product is swallowed, get medical help or contact a Poison Control Center right away.

- May stain some fabrics.

Directions

- apply liberally15 minutes before sun exposure
- reapply: after 80 minutes of swimming or sweating
- immediately after towel drying
- at least every 2 hours
- Sun Protection Measures: Spending time in the sun increases your risk of skin cancer and early skin aging. To decrease this risk, regularly use a sunscreen with a broad spectrum SPF of 15 or higher and other sun protection measures including:
- limit time in the sun, especially from 10 .am. to 2 p.m.
- wear long-sleeve shirts, pants, hats and sunglasses
- children under 6 months of age: Ask a doctor

Inactive Ingredients

Water, Hydrogenated Dimer Dilinoleyl/Dimethylcarbonate Copolymer, Stearyl Alcohol, Glycerin, Caprylyl Glycol, Cetyl Alcohol, Triethanolamine, Carbomer, Glyceryl Stearate, Behenyl Alcohol, Xanthan Gum, Sodium Lauroyl Sarcosinate, Disodium EDTA, Dipropylene Glycol, BHT, Disodium Ethylene Dicocamide PEG-15 Disulfate, Glyceryl Stearate Citrate, Cetearyl Alcohol, Sodium Lauroyl Lactylate, Retinyl Palmitate, Tocopheryl Acetate, Lecithin, Aloe Barbadensis Leaf Juice, Phenoxyethanol, Methyldibromo Glutaronitrile, Methylchloroisothiazolinone, Methylisothiazolinone.

Other information

- protect this product from excessive heat and direct sun

Principle Display Label

NDC 59054-880-10

Academy

SPORTS+OUTDOOR

SUNSCREEN LOTION

BROAD SPECTRUM

SPF 50

40

Water Resistant

(80 Minutes)

Hypoallergenic

UVA/UVB protection

16 FL. OZ.

(473 mL)